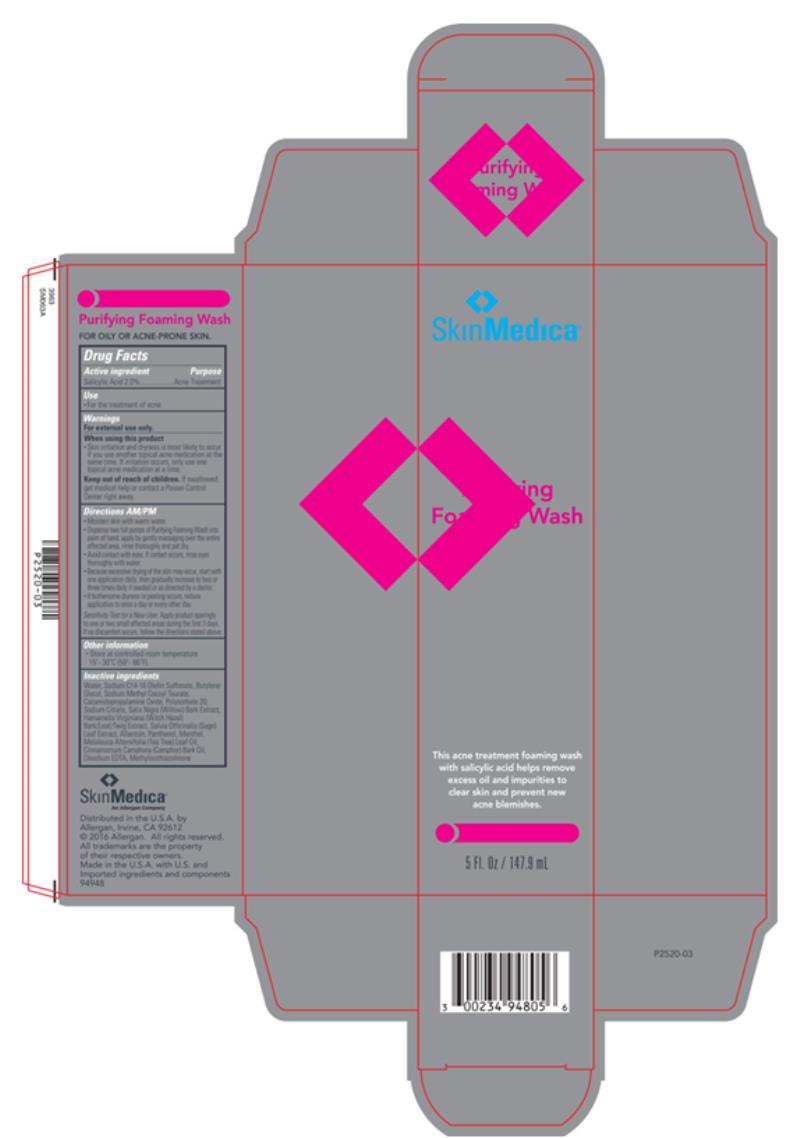 DRUG LABEL: SKIN MEDICA Purifying Foaming Wash
NDC: 0023-4948 | Form: LIQUID
Manufacturer: Allergan, Inc.
Category: otc | Type: HUMAN OTC DRUG LABEL
Date: 20130301

ACTIVE INGREDIENTS: salicylic acid 20 mg/1 mL
INACTIVE INGREDIENTS: ALLANTOIN; BUTYLENE GLYCOL; CAMPHOR OIL; COCAMIDOPROPYLAMINE OXIDE; EDETATE DISODIUM ANHYDROUS; HAMAMELIS VIRGINIANA TOP; TEA TREE OIL; MENTHOL, UNSPECIFIED FORM; METHYLISOTHIAZOLINONE; PANTHENOL; SALIX NIGRA BARK; SAGE; SODIUM C14-16 OLEFIN SULFONATE; SODIUM METHYL COCOYL TAURATE; POLYSORBATE 20; WATER; SODIUM CITRATE

Purifying Foaming Wash
Drug Facts

Active Ingredient

Salicylic Acid 2.0%

Purpose

Acne Treatment

Use

- For the treatment of acne.

Warnings

For external use only.

When using this product

- Skin irritation and dryness is most likely to occur if you use another topical acne medication at the same time. If irritation occurs, only use one topical acne medication at a time.

Keep out of reach of children.

If swallowed, get medical help or contact a Poison Control Center right away.

Directions AM/PM

- Moisten skin with warm water.
- Dispense two full pumps of Purifying Foaming Wash into palm of hand, apply by gently massaging over the entire affected area, rinse thoroughly and pat dry.
- Avoid contact with eyes. If contact occurs, rinse eyes thoroughly with water.
- Because excessive drying of the skin may occur, start with one application daily, then gradually increase to two or three times daily if needed or as directed by a doctor.
- If bothersome dryness or peeling occurs, reduce application to once a day or every other day.

Sensitivity Test for a New User. Apply product sparingly to one or two small affected areas during the first 3 days. If no discomfort occurs, follow the directions stated above.

Other information

- Store at controlled room temperature 15°- 30°C (59°- 86°F).

Inactive ingredients

Water, Sodium C14-16 Olefin Sulfonate, Butylene Glycol, Sodium Methyl Cocoyl Taurate, Cocamidopropylamine Oxide, Polysorbate 20, Sodium Citrate, Salix Nigra (Willow) Bark Extract, Hamamelis Virginiana (Witch Hazel) Bark/Leaf/Twig Extract, Salvia Officinalis (Sage) Leaf Extract, Allantoin, Panthenol, Menthol, Melaleuca Alternifolia (Tea Tree) Leaf Oil, Cinnamomum Camphora (Camphor) Bark Oil, Disodium EDTA, Methylisothiazolinone

Principal Display Panel

SkinMedica®

Purifying Foaming Wash

This acne treatment foaming wash
with salicylic acid helps remove
excess oil and impurities to
clear skin and prevent new
acne blemishes.

CLEANSE

5 Fl. Oz / 147.9 mL